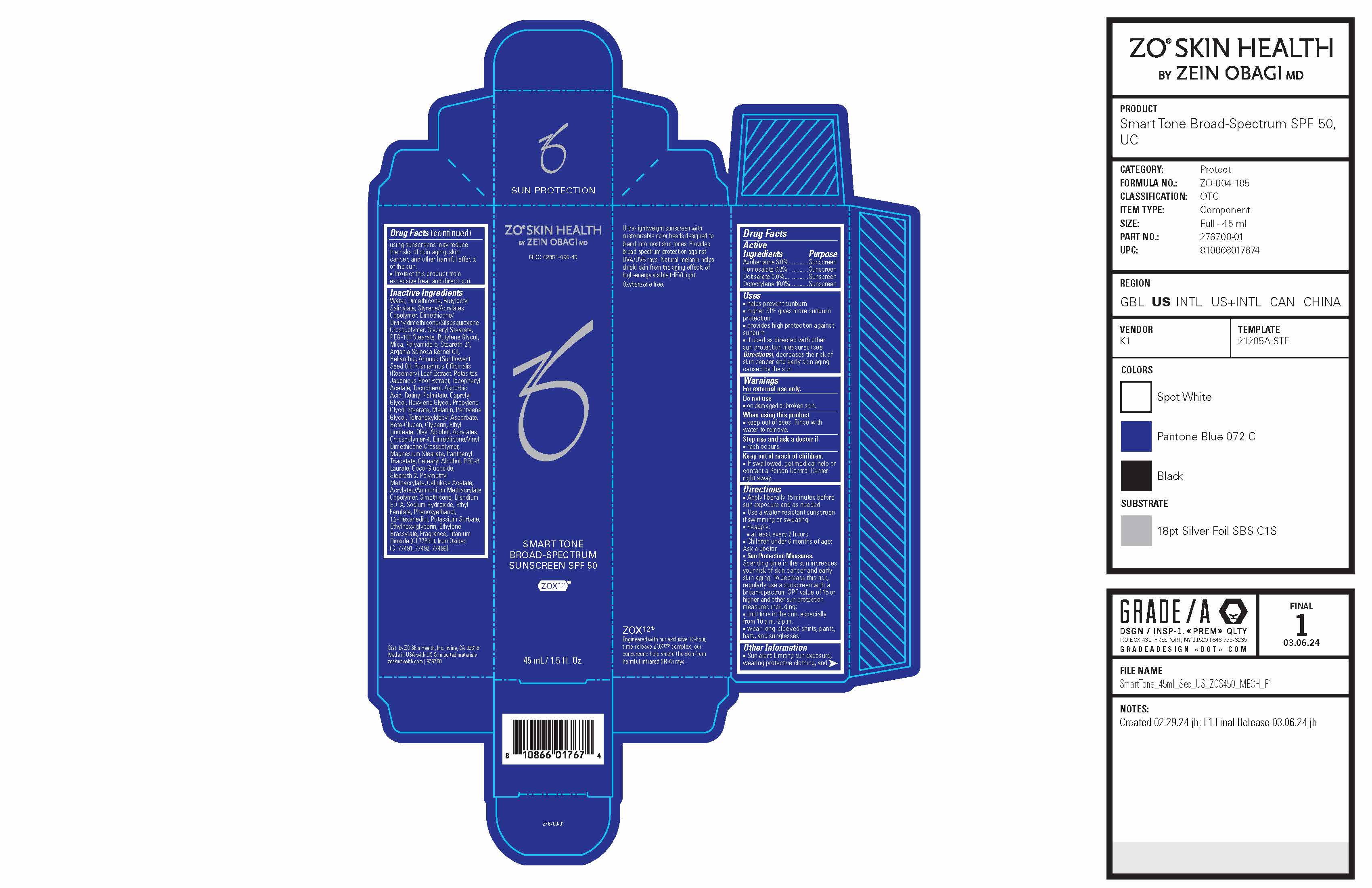 DRUG LABEL: ZO Skin Health Smart Tone Broad-Spectrum Sunscreen SPF 50
NDC: 42851-096 | Form: LOTION
Manufacturer: ZO Skin Health, Inc.
Category: otc | Type: HUMAN OTC DRUG LABEL
Date: 20241104

ACTIVE INGREDIENTS: OCTISALATE 50 mg/1 mL; AVOBENZONE 30 mg/1 mL; OCTOCRYLENE 100 mg/1 mL; HOMOSALATE 68 mg/1 mL
INACTIVE INGREDIENTS: PEG-100 STEARATE; CAPRYLYL GLYCOL; PROPYLENE GLYCOL STEARATE; CETOSTEARYL ALCOHOL; ETHYL FERULATE; PHENOXYETHANOL; ETHYL LINOLEATE; DIMETHICONE/VINYL DIMETHICONE CROSSPOLYMER (SOFT PARTICLE); MAGNESIUM STEARATE; 1,2-HEXANEDIOL; TITANIUM DIOXIDE; FERRIC OXIDE RED; ETHYLHEXYLGLYCERIN; TETRAHEXYLDECYL ASCORBATE; CELLULOSE ACETATE; SODIUM HYDROXIDE; ETHYLENE BRASSYLATE; PEG-8 LAURATE; OLEYL ALCOHOL; ACRYLATES CROSSPOLYMER-4; PANTHENOL TRIACETATE, (+)-; PETASITES JAPONICUS ROOT; BUTYLOCTYL SALICYLATE; ASCORBIC ACID; MICA; STEARETH-21; ROSEMARY; .ALPHA.-TOCOPHEROL ACETATE; VITAMIN A PALMITATE; HEXYLENE GLYCOL; MELANIN SYNTHETIC (TYROSINE, PEROXIDE); PENTYLENE GLYCOL; GLYCERIN; COCO-GLUCOSIDE; STEARETH-2; POLY(METHYL METHACRYLATE; 450000 MW); EDETATE DISODIUM; POTASSIUM SORBATE; WATER; POLYAMIDE-5; ARGAN OIL; SUNFLOWER OIL; TOCOPHEROL; DIMETHICONE/DIVINYLDIMETHICONE/SILSESQUIOXANE CROSSPOLYMER; BUTYLENE GLYCOL; DIMETHICONE

Drug Facts

Active Ingredients

Ingredients | Purpose
Avobenzone 3.0%............. | Sunscreen
Homosalate 6.8%............. | Sunscreen
Octisalate 5.0%................ | Sunscreen
Octocrylene 10.0%................ | Sunscreen

Uses

- helps prevent sunburn
- higher SPF gives more sunburn protection
- provides high protection against sunburn
- if used as directed with other sun protection measures (see Directions), decreases the risk of skin cancer and early skin aging caused by the sun

Warnings

For external use only.

Do not use

- on damaged or broken skin.

When using this product

- keep out of eyes. Rinse with water to remove.

Stop use and ask a doctor if

- rash occurs.

Keep out of reach of children.

- If swallowed, get medical help or contact a Poison Control Center right away.

Directions

- Apply liberally 15 minutes before sun exposure and as needed.
- Use a water-resistant sunscreen if swimming or sweating.
- Reapply: ■ at least every 2 hours ■ Children under 6 months of age: Ask a doctor.
- Sun Protection Measures. Spending time in the sun increases your risk of skin cancer and early skin aging. To decrease this risk, regularly use a sunscreen with a broad-spectrum SPF value of 15 or higher and other sun protection measures including: ■ limit time in the sun, especially from 10 a.m.-2 p.m. ■ wear long-sleeved shirts, pants, hats, and sunglasses.

Other Information

- Sun alert: Limiting sun exposure, wearing protective clothing, and using sunscreens may reduce the risks of skin aging, skin cancer, and other harmful effects of the sun.
- Protect this product from excessive heat and direct sun.

Inactive Ingredients

Water, Dimethicone, Butyloctyl Salicylate, Styrene/Acrylates Copolymer, Dimethicone/Divinyldimethicone/Silsesquioxane Crosspolymer, Glyceryl Stearate, PEG-100 Stearate, Butylene Glycol, Mica, Polyamide-5, Steareth-21, Argania Spinosa Kernel Oil, Helianthus Annuus (Sunflower) Seed Oil, Rosmarinus Officinalis (Rosemary) Leaf Extract, Petasites Japonicus Root Extract, Tocopheryl Acetate, Tocopherol, Ascorbic Acid, Retinyl Palmitate, Caprylyl Glycol, Hexylene Glycol, Propylene Glycol Stearate, Melanin, Pentylene Glycol, Tetrahexyldecyl Ascorbate, Beta-Glucan, Glycerin, Ethyl Linoleate, Oleyl Alcohol, Acrylates Crosspolymer-4, Dimethicone/Vinyl Dimethicone Crosspolymer, Magnesium Stearate, Panthenyl Triacetate, Cetearyl Alcohol, PEG-8 Laurate, Coco-Glucoside, Steareth-2, Polymethyl Methacrylate, Cellulose Acetate,Acrylates/Ammonium Methacrylate Copolymer, Simethicone, Disodium EDTA, Sodium Hydroxide, Ethyl Ferulate, Phenoxyethanol, 1,2-Hexanediol, Potassium Sorbate, Ethylhexylglycerin, Ethylene Brassylate, Fragrance, Titanium Dioxide (CI 77891), Iron Oxides (CI 77491, 77492, 77499).

PACKAGE LABEL

ZO® SKIN HEALTH

by ZEIN OBAGI MD

NDC 42851-096-45

Smart Tone Broad-Spectrum Sunscreen SPF 50

ZOX12 ®

45 mL / 1.5 Fl. Oz.